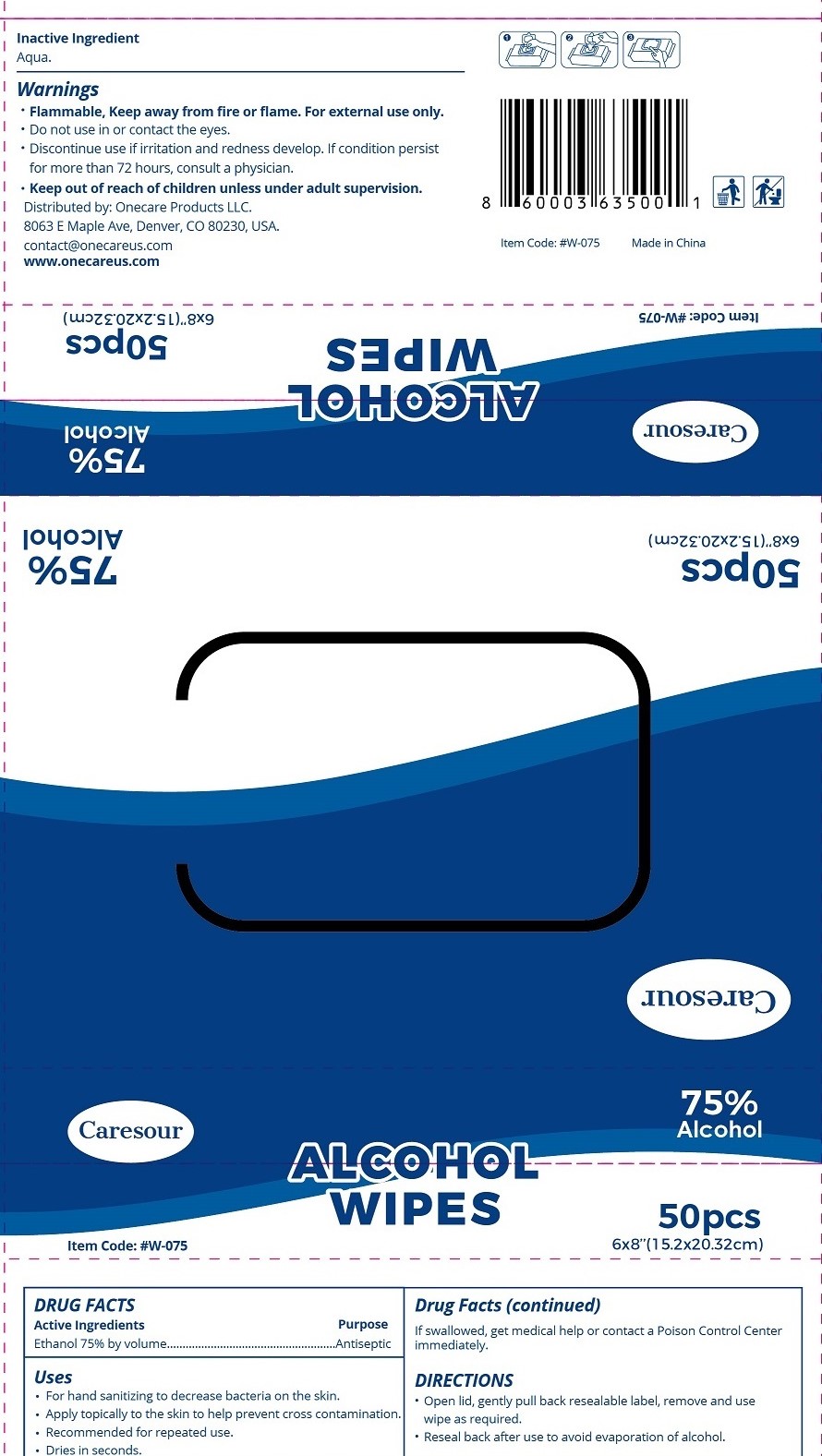 DRUG LABEL: Wet Wipe
NDC: 75513-001 | Form: SWAB
Manufacturer: Onecare Products LLC
Category: otc | Type: HUMAN OTC DRUG LABEL
Date: 20200417

ACTIVE INGREDIENTS: ALCOHOL 0.13 g/100 g
INACTIVE INGREDIENTS: WATER

wet wipes 75% Alcohol

Active Ingredient

Ethanol 75%

Purpose

Antiseptic

USE

For hand sanitizing to decrease bacteria on the skin.

Apply topically to the skin to help prevent cross contamination.
Recommended for repeated use.
Dries in seconds.

If swallowed, get medical help or contact a Poison Control Center
immediately.

Warning

●Flammable, Keep away from fire or flame. For external use only.
Do not use in or contact the eyes.
●Discontinue use if rritation and redness develop. If condition persist
for more than 72 hours, consult a physician.

●. Keep out of reach of children unless under adult supervision.

Directions

●Open lid, gently pull back resealable label, remove and use
wipe as required.
●Reseal back after use to avoid evaporation of alcohol.

Inactive ingredients

Aqua